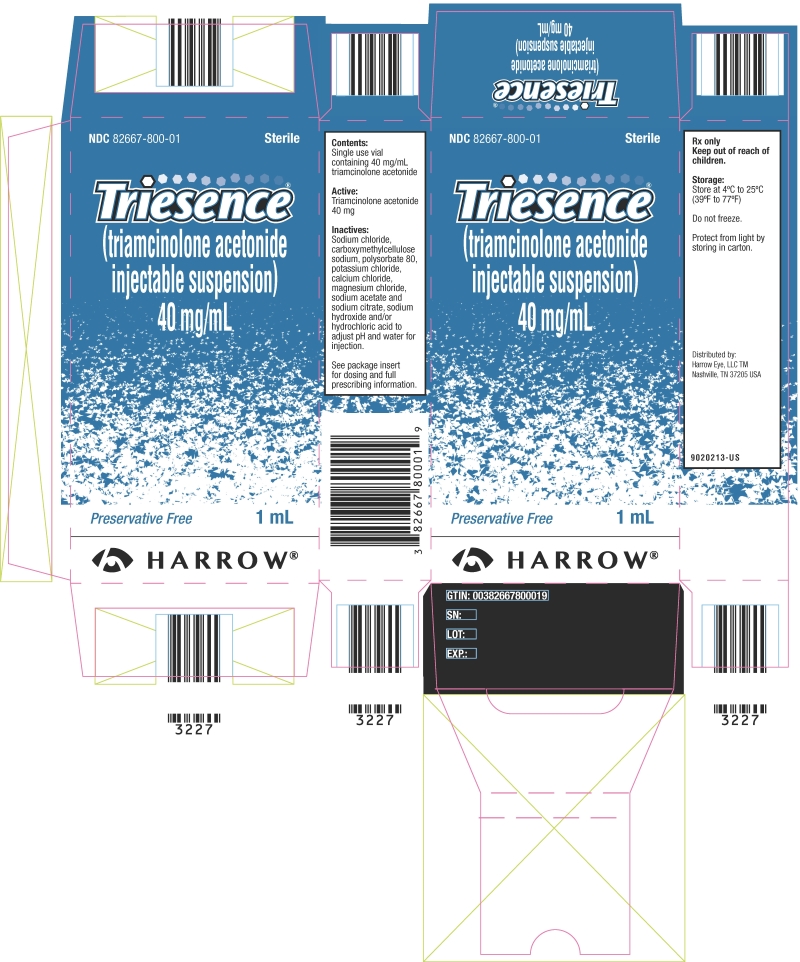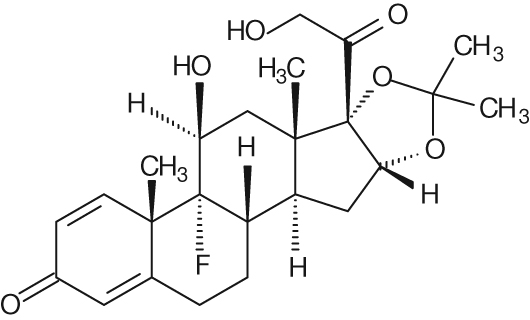 DRUG LABEL: TRIESENCE
NDC: 82667-800 | Form: INJECTION, SUSPENSION
Manufacturer: Harrow Eye, LLC
Category: prescription | Type: HUMAN PRESCRIPTION DRUG LABEL
Date: 20251030

ACTIVE INGREDIENTS: TRIAMCINOLONE ACETONIDE 40 mg/1 mL
INACTIVE INGREDIENTS: SODIUM CHLORIDE; CARBOXYMETHYLCELLULOSE SODIUM; POLYSORBATE 80; POTASSIUM CHLORIDE; CALCIUM CHLORIDE; MAGNESIUM CHLORIDE; SODIUM ACETATE; SODIUM CITRATE; WATER; SODIUM HYDROXIDE; HYDROCHLORIC ACID

HIGHLIGHTS OF PRESCRIBING INFORMATION

These highlights do not include all the information needed to use TRIESENCE (triamcinolone acetonide injectable suspension) 40 mg/mL safely and effectively. See full prescribing information for TRIESENCE suspension.
TRIESENCE®(triamcinolone acetonide injectable suspension) 40 mg/mL
Initial U.S. Approval: 1957

1 INDICATIONS AND USAGE

TRIESENCEsuspension is a synthetic corticosteroid indicated for:

• Treatment of the following ophthalmic diseases: sympathetic ophthalmia, temporal arteritis, uveitis, and ocular inflammatory conditions unresponsive to topical corticosteroids. (1.1)

• Visualization during vitrectomy. (1.2)

2 DOSAGE AND ADMINISTRATION

• Initial recommended dose for all indications except visualization: 4 mg (100 microliters of 40 mg/mL suspension) with subsequent dosage as needed over the course of treatment. (2.1)

• Recommended dose for visualization: 1 to 4 mg (25 to 100 microliters of 40 mg/mL suspension) administered intravitreally. (2.2)

3 DOSAGE FORMS AND STRENGTHS

Single use 1 mL vial containing 40 mg/mL of triamcinolone acetonide suspension. (3)

4 CONTRAINDICATIONS

• Patients with systemic fungal infections. (4)

• Hypersensitivity to triamcinolone or any component of this product. (4)

5 WARNINGS AND PRECAUTIONS

• TRIESENCE suspension should not be administered intravenously. (5.1)

• Ophthalmic Effects: May include cataracts, infections, and glaucoma. Monitor intraocular pressure (IOP). (5.1)

• Hypothalamic-pituitary-adrenal (HPA) axis suppression, Cushing's syndrome and hyperglycemia: Monitor patients for these conditions and taper doses gradually. (5.2)

• Infections: Increased susceptibility to new infection and increased risk of exacerbation, dissemination, or reactivation of latent infection. (5.3)

• Elevated blood pressure, salt and water retention, and hypokalemia: Monitor blood pressure and sodium, potassium serum levels. (5.4)

• GI perforation: Increased risk in patients with certain GI disorders. (5.5)

• Behavioral and mood disturbances: May include euphoria, insomnia, mood swings, personality changes, severe depression, and psychosis. (5.6)

• Decreases in bone density: Monitor bone density in patients receiving long term corticosteroid therapy. (5.7)

• Live or live attenuated vaccines: Do not administer to patients receiving immunosuppressive doses of corticosteroids. (5.8)

• Negative effects on growth and development: Monitor pediatric patients on long-term corticosteroid therapy. (5.9)

• Use in pregnancy: Fetal harm can occur with first trimester use. (5.10)

• Weight gain: May cause increased appetite. (5.11)

To report SUSPECTED ADVERSE REACTIONS, contact Harrow Eye, LLC at 833-4HARROW(427769) or FDA at 1-800-FDA-1088 orwww.fda.gov/medwatch.

7 DRUG INTERACTIONS

• Anticoagulant agents: May enhance or diminish anticoagulant effects. Monitor coagulation indices. (7)

• Antidiabetic agents: May increase blood glucose concentrations. Dose adjustments of antidiabetic agents may be required. (7)

• CYP 3A4 inducers and inhibitors: May respectively increase or decrease clearance of corticosteroids necessitating dose adjustment. (7)

• Non-steroidal anti inflammatory drugs (NSAIDs), including aspirin and salicylates: Increased risk of gastrointestinal side effects. (7)

FULL PRESCRIBING INFORMATION

1 INDICATIONS AND USAGE

1.1 Ophthalmic Diseases

TRIESENCE(triamcinolone acetonide injectable suspension) 40 mg/mL is indicated for:

• sympathetic ophthalmia,

• temporal arteritis,

• uveitis, and

• ocular inflammatory conditions unresponsive to topical corticosteroids.

1.2 Visualization During Vitrectomy

TRIESENCE suspension is indicated for visualization during vitrectomy.

2 DOSAGE AND ADMINISTRATION

2.1 Dosage for Treatment of Ophthalmic Diseases

The initial recommended dose of TRIESENCEsuspension is 4 mg (100 microliters of 40 mg/mL suspension) with subsequent dosage as needed over the course of treatment.

2.2 Dosage for Visualization During Vitrectomy

The recommended dose of TRIESENCE®suspension is 1 to 4 mg (25 to 100 microliters of 40 mg/mL suspension) administered intravitreally.

2.3 Preparation for Administration

STRICT ASEPTIC TECHNIQUE IS MANDATORY.The vial should be vigorously shaken for 10 seconds before use to ensure a uniform suspension. Prior to withdrawal, the suspension should be inspected for clumping or granular appearance (agglomeration). An agglomerated product results from exposure to freezing temperatures and should not be used. After withdrawal, TRIESENCEsuspension should be injected without delay to prevent settling in the syringe. Careful technique should be employed to avoid the possibility of entering a blood vessel or introducing organisms that can cause infection.

2.4 Administration

The injection procedure should be carried out under controlled aseptic conditions, which include the use of sterile gloves, a sterile drape, and a sterile eyelid speculum (or equivalent). Adequate anesthesia and a broad-spectrum microbicide should be given prior to the injection.

Following the injection, patients should be monitored for elevation in intraocular pressure (IOP) and for endophthalmitis. Monitoring may consist of a check for perfusion of the optic nerve head immediately after the injection, tonometry within 30 minutes following the injection, and biomicroscopy between two and seven days following the injection. Patients should be instructed to report any symptoms suggestive of endophthalmitis without delay.

Each vial should only be used for the treatment of a single eye. If the contralateral eye requires treatment, a new vial should be used and the sterile field, syringe, gloves, drapes, eyelid speculum, and injection needles should be changed before TRIESENCEsuspension is administered to the other eye.

3 DOSAGE FORMS AND STRENGTHS

Single use 1 mL vial containing 40 mg/mL of sterile triamcinolone acetonide suspension.

4 CONTRAINDICATIONS

Corticosteroids are contraindicated in patients with systemic fungal infections.

Triamcinolone is contraindicated in patients who are hypersensitive to corticosteroids or any components of this product. Rare instances of anaphylactoid reactions have occurred in patients receiving corticosteroid therapy. [ see Adverse Reactions (6)].

5 WARNINGS AND PRECAUTIONS

5.1 Ophthalmic Effects

TRIESENCEsuspension should not be administered intravenously. Strict aseptic technique is mandatory.

Risk of infection

Corticosteroids may mask some signs of infection, and new infections may appear during their use. There may be decreased resistance and inability to localize infection when corticosteroids are used.

Corticosteroids may enhance the establishment of secondary ocular infections due to fungi or viruses. If an infection occurs during corticosteroid therapy, it should be promptly controlled by suitable antimicrobial therapy [ see Warnings and Precautions (5.3)] .

Elevated Intraocular Pressure

Increases in IOP associated with triamcinolone acetonide injection have been observed in 20% to 60% of patients. This may lead to glaucoma with possible damage to the optic nerve. Effects on IOP may last up to 6 months following injection and are usually managed by topical glaucoma therapy. A small percentage of patients may require aggressive non-topical treatment. Intraocular pressure as well as perfusion of the optic nerve head should be monitored and managed appropriately.

Endophthalmitis

The rate of infectious culture positive endophthalmitis is 0.5%. Proper aseptic techniques should always be used when administering triamcinolone acetonide. In addition, patients should be monitored following the injection to permit early treatment should an infection occur.

Cataracts

Use of corticosteroids may produce cataracts, particularly posterior subcapsular cataracts.

Patients with Ocular Herpes Simplex

Corticosteroids should be used cautiously in patients with ocular herpes simplex because of possible corneal perforation. Corticosteroids should not be used in activeocular herpes simplex.

5.2 Alterations in Endocrine Function

Hypothalamic-pituitary-adrenal (HPA) axis suppression, Cushing's syndrome, and hyperglycemia. Monitor patients for these conditions with chronic use.

Corticosteroids can produce reversible HPA axis suppression with the potential for glucocorticosteroid insufficiency after withdrawal of treatment. Drug induced secondary adrenocortical insufficiency may be minimized by gradual reduction of dosage. This type of relative insufficiency may persist for months after discontinuation of therapy; therefore, in any situation of stress occurring during that period, hormone therapy should be reinstituted.

Metabolic clearance of corticosteroids is decreased in hypothyroid patients and increased in hyperthyroid patients. Changes in thyroid status of the patient may necessitate adjustment in dosage.

5.3 Increased Risks Related to Infections

Corticosteroids may increase the risks related to infections with any pathogen, including viral, bacterial, fungal, protozoan, or helminthic infections. The degree to which the dose, route and duration of corticosteroid administration correlates with the specific risks of infection is not well characterized; however, with increasing doses of corticosteroids, the rate of occurrence of infectious complications increases.

Corticosteroids may mask some signs of infection and may reduce resistance to new infections.

Corticosteroids may exacerbate infections and increase risk of disseminated infection. The use of corticosteroids in active tuberculosis should be restricted to those cases of fulminating or disseminated tuberculosis in which the corticosteroid is used for the management of the disease in conjunction with an appropriate antituberculous regimen.

Chickenpox and measles can have a more serious or even fatal course in non-immune children or adults on corticosteroids. In children or adults who have not had these diseases, particular care should be taken to avoid exposure. If a patient is exposed to chickenpox, prophylaxis with varicella zoster immune globulin (VZIG) may be indicated. If patient is exposed to measles, prophylaxis with pooled intramuscular immunoglobulin (IG) may be indicated. If chickenpox develops, treatment with antiviral agents may be considered.

Corticosteroids should be used with great care in patients with known or suspected Strongyloides (threadworm) infestation. In such patients, corticosteroid-induced immunosuppression may lead to Strongyloides hyperinfection and dissemination with widespread larval migration, often accompanied by severe enterocolitis and potentially fatal gram-negative septicemia.

Corticosteroids may increase risk of reactivation or exacerbation of latent infection. If corticosteroids are indicated in patients with latent tuberculosis or tuberculin reactivity, close observation is necessary as reactivation of the disease may occur. During prolonged corticosteroid therapy, these patients should receive chemoprophylaxis.

Corticosteroids may activate latent amebiasis. Therefore, it is recommended that latent or active amebiasis be ruled out before initiating corticosteroid therapy in any patient who has spent time in the tropics or in any patient with unexplained diarrhea.

Corticosteroids should not be used in cerebral malaria.

5.4 Alterations in Cardiovascular/Renal Function

Corticosteroids can cause elevation of blood pressure, salt and water retention, and increased excretion of potassium and calcium. These effects are less likely to occur with the synthetic derivatives except when used in large doses. Dietary salt restriction and potassium supplementation may be necessary. These agents should be used with caution in patients with hypertension, congestive heart failure, or renal insufficiency.

Literature reports suggest an association between use of corticosteroids and left ventricular free wall rupture after a recent myocardial infarction; therefore, therapy with corticosteroids should be used with caution in these patients.

5.5 Use in Patients With Gastrointestinal Disorders

There is an increased risk of gastrointestinal perforation in patients with certain GI disorders. Signs of GI perforation, such as peritoneal irritation, may be masked in patients receiving corticosteroids.

Corticosteroids should be used with caution if there is a probability of impending perforation, abscess or other pyogenic infections; diverticulitis; fresh intestinal anastomoses; and active or latent peptic ulcer.

5.6 Behavioral and Mood Disturbances

Corticosteroid use may be associated with central nervous system effects ranging from euphoria, insomnia, mood swings, personality changes, and severe depression, to frank psychotic manifestations. Also, existing emotional instability or psychotic tendencies may be aggravated by corticosteroids.

5.7 Decrease in Bone Density

Corticosteroids decrease bone formation and increase bone resorption both through their effect on calcium regulation (i.e., decreasing absorption and increasing excretion) and inhibition of osteoblast function. This, together with a decrease in the protein matrix of the bone secondary to an increase in protein catabolism, and reduced sex hormone production, may lead to inhibition of bone growth in children and adolescents and the development of osteoporosis at any age. Special consideration should be given to patients at increased risk of osteoporosis (i.e., postmenopausal women) before initiating corticosteroid therapy and bone density should be monitored in patients on long term corticosteroid therapy.

5.8 Vaccination

Administration of live or live attenuated vaccines is contraindicated in patients receiving immunosuppressive doses of corticosteroids. Killed or inactivated vaccines may be administered; however, the response to such vaccines cannot be predicted. Immunization procedures may be undertaken in patients who are receiving corticosteroids as replacement therapy, e.g., for Addison's disease.

While on corticosteroid therapy, patients should not be vaccinated against smallpox. Other immunization procedures should not be undertaken in patients who are on corticosteroids, especially on high dose, because of possible hazards of neurological complications and a lack of antibody response.

5.9 Effect on Growth and Development

Long-term use of corticosteroids can have negative effects on growth and development in children. Growth and development of pediatric patients on prolonged corticosteroid therapy should be carefully monitored.

5.10 Use in Pregnancy

Triamcinolone acetonide can cause fetal harm when administered to a pregnant woman. Human and animal studies suggest that use of corticosteroids during the first trimester of pregnancy is associated with an increased risk of orofacial clefts, intrauterine growth restriction and decreased birth weight. If this drug is used during pregnancy, or if the patient becomes pregnant while using this drug, the patient should be apprised of the potential hazard to the fetus [see Use in Specific Populations (8.1)].

5.11 Weight Gain

Systemically administered corticosteroids may increase appetite and cause weight gain.

5.12 Neuromuscular Effects

Although controlled clinical trials have shown corticosteroids to be effective in speeding the resolution of acute exacerbations of multiple sclerosis, they do not show that they affect the ultimate outcome or natural history of the disease. The studies do show that relatively high doses of corticosteroids are necessary to demonstrate a significant effect.

An acute myopathy has been observed with the use of high doses of corticosteroids, most often occurring in patients with disorders of neuromuscular transmission (e.g., myasthenia gravis), or in patients receiving concomitant therapy with neuromuscular blocking drugs (e.g., pancuronium). This acute myopathy is generalized, may involve ocular and respiratory muscles, and may result in quadriparesis. Elevation of creatine kinase may occur. Clinical improvement or recovery after stopping corticosteroids may require weeks to years.

5.13 Kaposi's Sarcoma

Kaposi's sarcoma has been reported to occur in patients receiving corticosteroid therapy, most often for chronic conditions. Discontinuation of corticosteroids may result in clinical improvement.

6 ADVERSE REACTIONS

Because clinical trials are conducted under widely varying conditions, adverse reaction rates observed in the clinical trials of a drug cannot be directly compared to rates in the clinical trials of another drug and may not reflect the rates observed in practice.

Adverse event data were collected from 300 published articles containing data from controlled and uncontrolled clinical trials which evaluated over 14000 eyes treated with different concentrations of triamcinolone acetonide. The most common dose administered within these trials was triamcinolone acetonide 4 mg administered as primary or adjunctive therapy primarily as a single injection.

The most common reported adverse events following administration of triamcinolone acetonide were elevated IOP and cataract progression. These events have been reported to occur in 20% to 60% of patients.

Less common reactions occurring in up to 2% include endophthalmitis (infectious and non-infectious), hypopyon, injection site reactions (described as blurring and transient discomfort), glaucoma, vitreous floaters, and detachment of retinal pigment epithelium, optic disc vascular disorder, eye inflammation, conjunctival hemorrhage, and visual acuity reduced. Cases of exophthalmos have also been reported.

Common adverse reactions for systemically administered corticosteroids include fluid retention, alteration in glucose tolerance, elevation in blood pressure, behavioral and mood changes, increased appetite, and weight gain.

Other reactions reported to have occurred with the administration of corticosteroids include:

Allergic Reactions:Anaphylactoid reaction, anaphylaxis, angioedema

Cardiovascular:Bradycardia, cardiac arrest, cardiac arrhythmias, cardiac enlargement, circulatory collapse, congestive heart failure, fat embolism, hypertrophic cardiomyopathy in premature infants, myocardial rupture following recent myocardial infarction, pulmonary edema, syncope, tachycardia, thromboembolism, thrombophlebitis, vasculitis

Dermatologic:Acne, allergic dermatitis, cutaneous and subcutaneous atrophy, dry scalp, edema, facial erythema, hyper or hypo-pigmentation, impaired wound healing, increased sweating, petechiae and ecchymoses, rash, sterile abscess, striae, suppressed reactions to skin tests, thin fragile skin, thinning scalp hair, urticaria

Endocrine:Abnormal fat deposits, decreased carbohydrate tolerance, development of Cushingoid state, hirsutism, manifestations of latent diabetes mellitus and increased requirements for insulin or oral hypoglycemic agents in diabetics, menstrual irregularities, moon facies, secondary adrenocortical and pituitary unresponsiveness (particularly in times of stress, as in trauma, surgery or illness), suppression of growth in children

Fluid and Electrolyte Disturbances:Potassium loss, hypokalemic alkalosis, sodium retention

Gastrointestinal:Abdominal distention, elevation in serum liver enzymes levels (usually reversible upon discontinuation), hepatomegaly, hiccups, malaise, nausea, pancreatitis, peptic ulcer with possible perforation and hemorrhage, ulcerative esophagitis

Metabolic:Negative nitrogen balance due to protein catabolism

Musculoskeletal:Aseptic necrosis of femoral and humeral heads, charcot-like arthropathy, loss of muscle mass, muscle weakness, osteoporosis, pathologic fracture of long bones, steroid myopathy, tendon rupture, vertebral compression fractures

Neurological:Arachnoiditis, convulsions, depression, emotional instability, euphoria, headache, increased intracranial pressure with papilledema (pseudo-tumor cerebri) usually following discontinuation of treatment, insomnia, meningitis, neuritis, neuropathy, paraparesis/paraplegia, paresthesia, sensory disturbances, vertigo

Reproductive:Alteration in motility and number of spermatozoa

7 DRUG INTERACTIONS

• Amphotericin B:There have been cases reported in which concomitant use of Amphotericin B and hydrocortisone was followed by cardiac enlargement and congestive heart failure (s ee Potassium Depleting Agents).

• Anticholinesterase agents:Concomitant use of anticholinesterase agents and corticosteroids may produce severe weakness in patients with myasthenia gravis. If possible, anticholinesterase agents should be withdrawn at least 24 hours before initiating corticosteroid therapy.

• Anticoagulant agents:Coadministration of corticosteroids and warfarin usually results in inhibition of response to warfarin, although there have been some conflicting reports. Therefore, coagulation indices should be monitored frequently to maintain the desired anticoagulant effect.

• Antidiabetic agents:Because corticosteroids may increase blood glucose concentrations, dosage adjustments of antidiabetic agents may be required.

• Antitubercular drugs:Serum concentrations of isoniazid may be decreased.

• CYP 3A4 inducers (e.g., barbiturates, phenytoin, carbamazepine, and rifampin):Drugs, such as barbiturates, phenytoin, ephedrine, and rifampin, which induce hepatic microsomal drug metabolizing enzyme activity may enhance metabolism of corticosteroid and require that the dosage of corticosteroid be increased.

• CYP 3A4 inhibitors (e.g., ketoconazole, macrolide antibiotics):Ketoconazole has been reported to decrease the metabolism of certain corticosteroids by up to 60% leading to an increased risk of corticosteroid side effects.

• Cholestyramine:Cholestyramine may increase the clearance of corticosteroids.

• Cyclosporine:Increased activity of both cyclosporine and corticosteroids may occur when the two are used concurrently. Convulsions have been reported with concurrent use.

• Digitalis:Patients on digitalis glycosides may be at increased risk of arrhythmias due to hypokalemia.

• Estrogens, including oral contraceptives:Estrogens may decrease the hepatic metabolism of certain corticosteroids thereby increasing their effect.

• NSAIDs including aspirin and salicylates:Concomitant use of aspirin or other non-steroidal antiinflammatory agents and corticosteroids increases the risk of gastrointestinal side effects. Aspirin should be used cautiously in conjunction with corticosteroids in hypoprothrombinemia. The clearance of salicylates may be increased with concurrent use of corticosteroids.

• Potassium depleting agents (e.g., diuretics, Amphotericin B):When corticosteroids are administered concomitantly with potassium-depleting agents, patients should be observed closely for development of hypokalemia.

• Skin tests:Corticosteroids may suppress reactions to skin tests.

• Toxoids and live or inactivated vaccines:Due to inhibition of antibody response, patients on prolonged corticosteroid therapy may exhibit a diminished response to toxoids and live or inactivated vaccines. Corticosteroids may also potentiate the replication of some organisms contained in live attenuated vaccines.

8 USE IN SPECIFIC POPULATIONS

8.1 Pregnancy

Teratogenic Effects: Pregnancy Category D [see Warnings and Precautions (5.10)]

Multiple cohort and case controlled studies in humans suggest that maternal corticosteroid use during the first trimester increases the rate of cleft lip with or without cleft palate from about 1/1000 infants to 3- 5/1000 infants. Two prospective case control studies showed decreased birth weight in infants exposed to maternal corticosteroids in utero.

Triamcinolone acetonide was teratogenic in rats, rabbits, and monkeys. In rats and rabbits, triamcinolone acetonide was teratogenic at inhalation doses of 0.02 mg/kg and above and in monkeys, triamcinolone acetonide was teratogenic at an inhalation dose of 0.5 mg/kg (1/4 and 7 times the recommended human dose). Dose-related teratogenic effects in rats and rabbits included cleft palate and/or internal hydrocephaly and axial skeletal defects, whereas the effects observed in monkeys were cranial malformations. These effects are similar to those noted with other corticosteroids.

Corticosteroids should be used during pregnancy only if the potential benefit justifies the potential risk to the fetus. Infants born to mothers who received corticosteroids during pregnancy should be carefully observed for signs of hypoadrenalism.

8.3 Nursing Mothers

Corticosteroids are secreted in human milk. Reports suggest that steroid concentrations in human milk are 5% to 25% of maternal serum levels, and that total infant daily doses are small, less than 0.2% of the maternal daily dose. The risk of infant exposure to steroids through breast milk should be weighed against the known benefits of breastfeeding for both the mother and baby.

8.4 Pediatric Use

The efficacy and safety of corticosteroids in the pediatric population are based on the well established course of effect of corticosteroids which is similar in pediatric and adult populations.

The adverse effects of corticosteroids in pediatric patients are similar to those in adults. [see Adverse Reactions (6)] .

Like adults, pediatric patients should be carefully observed with frequent measurements of blood pressure, weight, height, IOP, and clinical evaluation for the presence of infection, psychosocial disturbances, thromboembolism, peptic ulcers, cataracts, and osteoporosis. Children, who are treated with corticosteroids by any route, including systemically administered corticosteroids, may experience a decrease in their growth velocity. This negative impact of corticosteroids on growth has been observed at low systemic doses and in the absence of laboratory evidence of HPA axis suppression (i.e., cosyntropin stimulation and basal cortisol plasma levels). Growth velocity may therefore be a more sensitive indicator of systemic corticosteroid exposure in children than some commonly used tests of HPA axis function. The linear growth of children treated with corticosteroids by any route should be monitored, and the potential growth effects of prolonged treatment should be weighed against clinical benefits obtained and the availability of other treatment alternatives. In order to minimize the potential growth effects of corticosteroids, children should be titrated to the lowest effective dose.

8.5 Geriatric Use

No overall differences in safety or effectiveness were observed between elderly subjects and younger subjects, and other reported clinical experience with triamcinolone has not identified differences in responses between the elderly and younger patients. However, the incidence of corticosteroid-induced side effects may be increased in geriatric patients and are dose-related. Osteoporosis is the most frequently encountered complication, which occurs at a higher incidence rate in corticosteroid-treated geriatric patients as compared to younger populations and in age-matched controls. Losses of bone mineral density appear to be greatest early on in the course of treatment and may recover over time after steroid withdrawal or use of lower doses.

11 DESCRIPTION

TRIESENCE(triamcinolone acetonide injectable suspension) 40 mg/mL is a synthetic corticosteroid with anti-inflammatory action. Each mL of the sterile, aqueous suspension provides 40 mg of triamcinolone acetonide, with sodium chloride for isotonicity, 0.5% (w/v) carboxymethylcellulose sodium and 0.015% polysorbate 80. It also contains calcium chloride (dihydrate), magnesium chloride (hexahydrate), potassium chloride, sodium acetate (trihydrate), sodium citrate (dihydrate) and water for injection. Sodium hydroxide and hydrochloric acid may be present to adjust pH to a target value 6 - 7.5.

The chemical name for triamcinolone acetonide is 9-Fluro- 11β, 16α, 17,21-tetrahydroxypregna-1,4-diene-3,20-dione cyclic 16,17- acetal with acetone. Its structural formula of C24H31FO6is:

434.50 g/mol Molecular Weight

Triamcinolone acetonide occurs as a white to cream-colored, crystalline powder having not more than a slight odor and is practically insoluble in water and very soluble in alcohol.

12 CLINICAL PHARMACOLOGY

12.1 Mechanism of Action

Naturally occurring glucocorticoids (hydrocortisone and cortisone), which also have salt-retaining properties, are used as replacement therapy in adrenocortical deficiency states. Their synthetic analogs, such as prednisolone and triamcinolone are primarily used for their anti-inflammatory effects in disorders of many organ systems.

Triamcinolone acetonide possesses glucocorticoid activity typical of this class of drug, but with little or no mineralocorticoid activity. For the purposes of comparison, the following is the equivalent milligram dosage of the various glucocorticoids:

Cortisone, 25 | Prednisone, 5 | Paramethasone, 2
Hydrocortisone, 20 | Methylprednisolone, 4 | Betamethasone, 0.75
Prednisolone, 5 | Triamcinolone, 4 | Dexamethasone, 0.75

Corticosteroids have been demonstrated to depress the production of eosinophils and lymphocytes, but erythropoiesis and production of polymorphonuclear leukocytes are stimulated. Inflammatory processes (edema, fibrin deposition, capillary dilatation, migration of leukocytes and phagocytosis) and the later stages of wound healing (capillary proliferation, deposition of collagen, cicatrization) are inhibited.

12.3 Pharmacokinetics

Aqueous humor pharmacokinetics of triamcinolone have been assessed in 5 patients following a single intravitreal administration (4 mg) of triamcinolone acetonide. Aqueous humor samples were obtained from 5 patients (5 eyes) via an anterior chamber paracentesis on Days 1, 3, 10, 17, and 31 postinjection. Peak aqueous humor concentrations of triamcinolone ranged from 2151 to 7202 ng/mL, half-life 76 to 635 hours, and the area under the concentration-time curve (AUC0-t) from 231 to 1911 ng.h/mL following the single intravitreal administration. The mean elimination half-life was 18.7 ± 5.7 days in 4 nonvitrectomized eyes (4 patients). In a patient who had undergone vitrectomy (1 eye), the elimination half-life of triamcinolone from the vitreous was much faster (3.2 days) relative to patients that had not undergone vitrectomy.

13 NONCLINICAL TOXICOLOGY

13.1 Carcinogenesis, Mutagenesis, Impairment of Fertility

No evidence of mutagenicity was detected from in vitro tests conducted with triamcinolone acetonide, including a reverse mutation test in Salmonella bacteria and a forward mutation test in Chinese hamster ovary cells. With regard to carcinogenicity, in a two-year study in rats, triamcinolone acetonide caused no treatment-related carcinogenicity at oral doses up to 0.001 mg/kg and in a two-year study in mice, triamcinolone acetonide caused no treatment-related carcinogenicity at oral doses up to 0.003 mg/kg (less than 1/25th of the recommended human dose). In male and female rats, triamcinolone acetonide caused no change in pregnancy rate at oral doses up to 0.015 mg/kg, but caused increased fetal resorptions and stillbirths and decreases in pup weight and survival at doses of 0.005 mg/kg (less than 1/10th of the recommended human dose).

13.2 Animal Toxicology and/or Pharmacology

Studies were conducted with triamcinolone acetonide, including those employing the proposed dosage form, i.e., 4.0% triamcinolone acetonide injectable suspension formulation containing 0.5% carboxymethylcellulose and 0.015% polysorbate-80 in a balanced salt solution.

Triamcinolone acetonide was demonstrated to be non-inflammatory when injected intravitreally in New Zealand White NZW rabbits, non-cytotoxic to mouse L-929 cells in an in vitro assay and non-sensitizing in a guinea-pig maximization assay. Furthermore, the results of single-dose intravitreal injection studies with triamcinolone acetonide in both rabbits and monkeys demonstrate that the drug is well tolerated for up to one month with only minor findings of slight decrease in body weight gain and slight corneal thinning.

16 HOW SUPPLIED/STORAGE AND HANDLING

TRIESENCE (triamcinolone acetonide injectable suspension) 40 mg/mL is supplied as 1 mL of a 40 mg/mL sterile triamcinolone acetonide suspension in a flint Type 1 single use glass vial with a gray rubber stopper and an open target aluminum seal. Each labeled vial is sealed in a polycarbonate blister with a backing material which provides tamper evidence and is stored in a carton.

• 1 mL single use vial NDC 82667-800-01

Storage

Store at 4°C to 25°C (39°F to 77°F); Do Not Freeze.Protect from light by storing in carton.

17 PATIENT COUNSELING INFORMATION

Patients should discuss with their physician if they have had recent or ongoing infections or if they have recently received a vaccine.

There are a number of medicines that can interact with corticosteroids, such as triamcinolone. Patients should inform their health-care provider of all the medicines they are taking, including over-the-counter and prescription medicines (such as phenytoin, diuretics, digitalis or digoxin, rifampin, amphotericin B, cyclosporine, insulin or diabetes medicines, ketoconazole, estrogens, including birth control pills and hormone replacement therapy, blood thinners, such as warfarin, aspirin or other NSAIDs, barbiturates), dietary supplements, and herbal products. If patients are taking any of these drugs, alternate therapy, dosage adjustment, and/or special test may be needed during the treatment.

Patients should be advised of common adverse reactions that could occur with corticosteroid use to include elevated IOP, cataracts, fluid retention, alteration in glucose tolerance, elevation in blood pressure, behavioral and mood changes, increased appetite and weight gain.

Distributed by:

Harrow Eye, LLC™

Nashville, TN 37205 USA

PACKAGE LABEL

NDC 82667-800-01 Sterile

Triesence®

(triamcinolone acetonide injectable suspension)

40 mg/mL

Preservative Free1 mL

HARROW®